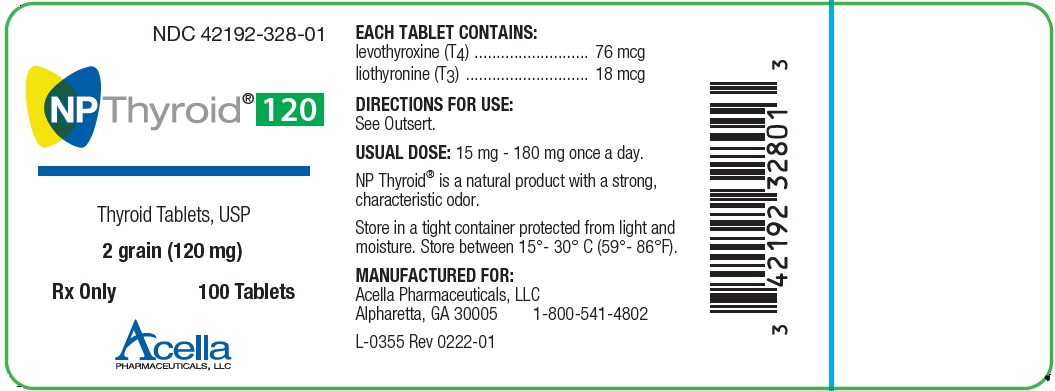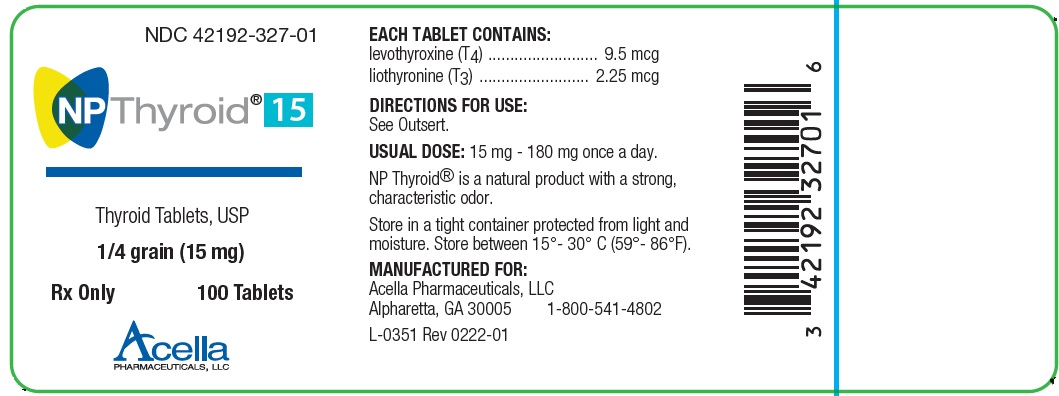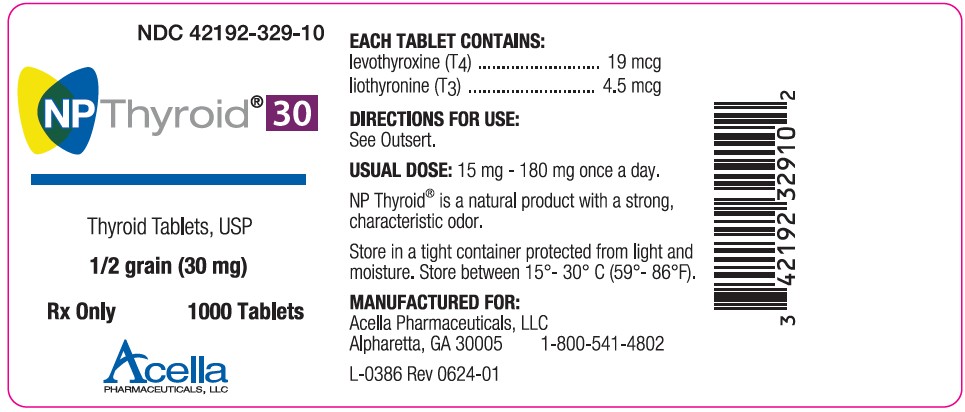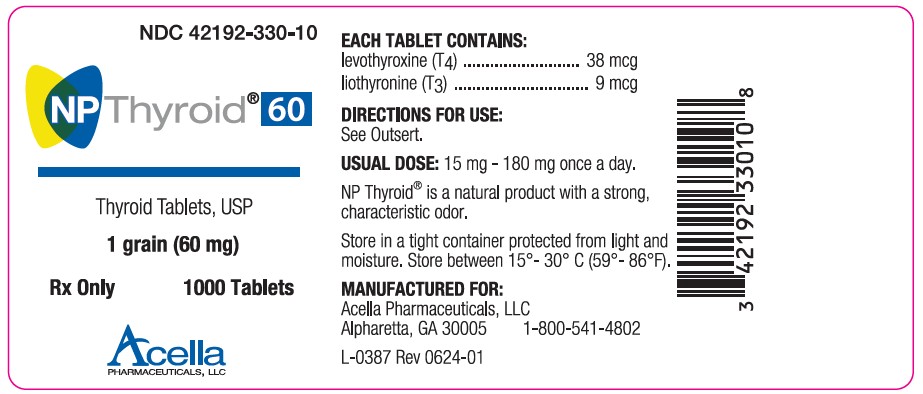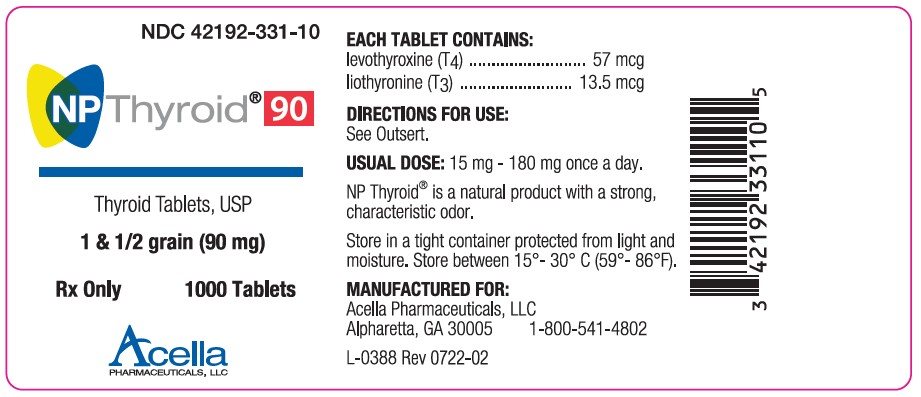 DRUG LABEL: NP Thyroid 15
NDC: 42192-327 | Form: TABLET
Manufacturer: Acella Pharmaceuticals, LLC
Category: prescription | Type: HUMAN PRESCRIPTION DRUG LABEL
Date: 20260127

ACTIVE INGREDIENTS: LIOTHYRONINE 2.25 ug/1 1; LEVOTHYROXINE 9.5 ug/1 1
INACTIVE INGREDIENTS: CALCIUM STEARATE; DEXTROSE MONOHYDRATE; MINERAL OIL

NP Thyroid®(THYROID TABLETS, USP)
Rx Only

DESCRIPTION

NP Thyroid®(thyroid tablets, USP) for oral use is a natural preparation derived from porcine thyroid glands. They contain both tetraiodothyronine sodium (T4levothyroxine) and triiodothyronine sodium (T3liothyronine) providing 38 mcg levothyroxine (T4) and 9 mcg liothyronine (T3) per grain of thyroid. The inactive ingredients are calcium stearate, dextrose (agglomerated) and mineral oil. Contains no ingredient made from a gluten-containing grain (wheat, barley, rye).

CLINICAL PHARMACOLOGY

The steps in the synthesis of the thyroid hormones are controlled by thyrotropin (Thyroid Stimulating Hormone, TSH) secreted by the anterior pituitary. This hormone’s secretion is in turn controlled by a feedback mechanism effected by the thyroid hormones themselves and by thyrotropin releasing hormone (TRH), a tripeptide of hypothalamic origin. Endogenous thyroid hormone secretion is suppressed when exogenous thyroid hormones are administered to euthyroid individuals in excess of the normal gland’s secretion.

The mechanisms by which thyroid hormones exert their physiologic action are not well understood. These hormones enhance oxygen consumption by most tissues of the body, increase the basal metabolic rate, and the metabolism of carbohydrates, lipids, and proteins. Thus, they exert a profound influence on every organ system in the body and are of particular importance in the development of the central nervous system.

The normal thyroid gland contains approximately 200 mcg of levothyroxine (T4) per gram of gland, and 15 mcg of liothyronine (T3) per gram. The ratio of these two hormones in the circulation does not represent the ratio in the thyroid gland, since about 80 % of peripheral liothyronine (T3) comes from monodeiodination of levothyroxine. Peripheral monodeiodination of levothyroxine at the 5 position (inner ring) also results in the formation of reverse liothyronine (T3), which is calorigenically inactive.

Liothyronine (T3) levels are low in the fetus and newborn, in old age, in chronic caloric deprivation, hepatic cirrhosis, renal failure, surgical stress, and chronic illnesses representing what has been called the “T3thyronine syndrome.”

PHARMACOKINETICS

Pharmacokinetics- Animal studies have shown that T4is only partially absorbed from the gastrointestinal tract. The degree of absorption is dependent on the vehicle used for its administration and by the character of the intestinal contents, the intestinal flora, including plasma protein, and soluble dietary factors, all of which bind thyroid and thereby make it unavailable for diffusion. Only 41% is absorbed when given in a gelatin capsule as opposed to a 74% absorption when given with an albumin carrier.

Depending on other factors, absorption has varied from 48 to 79% of the administered dose. Fasting increases absorption. Malabsorption syndromes, as well as dietary factors, (children’s soybean formula, concomitant use of anionic exchange resins such as cholestyramine) cause excessive fecal loss. T3is almost totally absorbed, 95% in 4 hours. The hormones contained in the natural preparations are absorbed in a manner similar to the synthetic hormones.

More than 99% of circulating hormones are bound to serum proteins, including thyroid-binding globulin (TBg), thyroid-binding prealbumin (TBPA), and albumin (TBa), whose capacities and affinities vary for the hormones. The higher affinity of levothyroxine (T4) for both TBg and TBPA as compared to triiodothyronine (T3) partially explains the higher serum levels and longer half-life of the former hormone. Both protein-bound hormones exist in reverse equilibrium with minute amounts of free hormone, the latter accounting for the metabolic activity.

Deiodination of levothyroxine (T4) occurs at a number of sites, including liver, kidney, and other tissues. The conjugated hormone, in the form of glucuronide or sulfate, is found in the bile and gut where it may complete an enterohepatic circulation. Eighty-five percent of levothyroxine (T4) metabolized daily is deiodinated.

INDICATIONS AND USAGE

NP Thyroid®tablets (thyroid tablets, USP) are indicated:

1. As replacement or supplemental therapy in patients with hypothyroidism of any etiology, except transient hypothyroidism during the recovery phase of subacute thyroiditis. This category includes cretinism, myxedema, and ordinary hypothyroidism in patients of any age (children, adults, the elderly), or state (including pregnancy); primary hypothyroidism resulting from functional deficiency, primary atrophy, partial or total absence of thyroid gland, or the effects of surgery, radiation, or drugs, with or without the presence of goiter; and secondary (pituitary), or tertiary (hypothalamic) hypothyroidism (See WARNINGS).

2. As pituitary TSH suppressants, in the treatment or prevention of various types of euthyroid goiters, including thyroid nodules, subacute or chronic lymphocytic thyroiditis (Hashimoto’s), multinodular goiter, and in the management of thyroid cancer.

CONTRAINDICATIONS

Thyroid hormone preparations are generally contraindicated in patients with diagnosed but as yet uncorrected adrenal cortical insufficiency, untreated thyrotoxicosis, and apparent hypersensitivity to any of their active or extraneous constituents. There is no well-documented evidence from the literature, however, of true allergic or idiosyncratic reactions to thyroid hormone.

WARNINGS

BOXED WARNING

Drugs with thyroid hormone activity, alone or together with other therapeutic agents, have been used for the treatment of obesity. In euthyroid patients, doses within the range of daily hormonal requirements are ineffective for weight reduction. Larger doses may produce serious or even life-threatening manifestations of toxicity, particularly when given in association with sympathomimetic amines such as those used for their anorectic effects.

The use of thyroid hormones in the therapy of obesity, alone or combined with other drugs, is unjustified and has been shown to be ineffective. Neither is their use justified for the treatment of male or female infertility unless this condition is accompanied by hypothyroidism.

PRECAUTIONS

General- Thyroid hormones should be used with great caution in a number of circumstances where the integrity of the cardiovascular system, particularly the coronary arteries, is suspected. These include patients with angina pectoris or the elderly, in whom there is a greater likelihood of occult cardiac disease. In these patients therapy should be initiated with low doses, i.e., 15-30 mg NP Thyroid®. When, in such patients, a euthyroid state can only be reached at the expense of an aggravation of the cardiovascular disease, thyroid hormone dosage should be reduced.

Thyroid hormone therapy in patients with concomitant diabetes mellitus or diabetes insipidus or adrenal cortical insufficiency aggravates the intensity of their symptoms. Appropriate adjustments of the various therapeutic measures directed at these concomitant endocrine diseases are required. The therapy of myxedema coma requires simultaneous administration of glucocorticoids (See DOSAGE AND ADMINISTRATION).

Hypothyroidism decreases and hyperthyroidism increases the sensitivity to oral anticoagulants. Prothrombin time should be closely monitored in thyroid-treated patients on oral anticoagulants and dosage of the latter agents adjusted on the basis of frequent prothrombin time determinations. In infants, excessive doses of thyroid hormone preparations may produce craniosynostosis.

PATIENT COUNSELING INFORMATION

Information for the Patient- Patients on thyroid hormone preparations and parents of children on thyroid therapy should be informed that:

1. Replacement therapy is to be taken essentially for life, with the exception of cases of transient hypothyroidism, usually associated with thyroiditis, and in those patients receiving a therapeutic trial of the drug.

2. They should immediately report during the course of therapy any signs or symptoms of thyroid hormone toxicity, e.g., chest pain, increased pulse rate, palpitations, excessive sweating, heat intolerance, nervousness, or any other unusual event.

3. In case of concomitant diabetes mellitus, the daily dosage of antidiabetic medication may need readjustment as thyroid hormone replacement is achieved. If thyroid medication is stopped, a downward readjustment of the dosage of insulin or oral hypoglycemic agent may be necessary to avoid hypoglycemia. At all times, close monitoring of urinary glucose levels is mandatory in such patients.

4. In case of concomitant oral anticoagulant therapy, the prothrombin time should be measured frequently to determine if the dosage of oral anticoagulants is to be readjusted.

5. Instruct patients to discontinue biotin or any biotin-containing supplements for at least 2 days before thyroid function testing is conducted.

6. Partial loss of hair may be experienced by children in the first few months of thyroid therapy, but this is usually a transient phenomenon and later recovery is usually the rule.

LABORATORY TESTS

Laboratory Tests- Treatment of patients with thyroid hormones requires the periodic assessment of thyroid status by means of appropriate laboratory tests besides the full clinical evaluation. The TSH suppression test can be used to test the effectiveness of any thyroid preparation bearing in mind the relative insensitivity of the infant pituitary to the negative feedback effect of thyroid hormones. Serum T4levels can be used to test the effectiveness of all thyroid medications except T3. When the total serum T4is low but TSH is normal, a test specific to assess unbound (free) T4levels is warranted. Specific measurements of T4and T3by competitive protein binding or radioimmunoassay are not influenced by blood levels of organic or inorganic iodine.

Drug Interactions

Oral Anticoagulants— Thyroid hormones appear to increase catabolism of vitamin K-dependent clotting factors. If oral anticoagulants are also being given, compensatory increases in clotting factor synthesis are impaired. Patients stabilized on oral anticoagulants who are found to require thyroid replacement therapy should be watched very closely when thyroid is started. If a patient is truly hypothyroid, it is likely that a reduction in anticoagulant dosage will be required. No special precautions appear to be necessary when oral anticoagulant therapy is begun in a patient already stabilized on maintenance thyroid replacement therapy.

Insulin or Oral Hypoglycemics— Initiating thyroid replacement therapy may cause increases in insulin or oral hypoglycemic requirements. The effects seen are poorly understood and depend upon a variety of factors such as dose and type of thyroid preparations and endocrine status of the patient. Patients receiving insulin or oral hypoglycemics should be closely watched during initiation of thyroid replacement therapy.

Cholestyramine or Colestipol- Cholestyramine or colestipol binds both T4and T3in the intestine, thus impairing absorption of these thyroid hormones. In vitrostudies indicate that the binding is not easily removed. Therefore, four to five hours should elapse between administration of cholestyramine and thyroid hormones.

Estrogen, Oral Contraceptives— Estrogens tend to increase serum thyroxine-binding globulin (TBg). In a patient with a nonfunctioning thyroid gland who is receiving thyroid replacement therapy, free levothyroxine may be decreased when estrogens are started thus increasing thyroid requirements. However, if the patient’s thyroid gland has sufficient function, the decreased free levothyroxine will result in a compensatory increase in levothyroxine output by the thyroid. Therefore, patients without a functioning thyroid gland who are on thyroid replacement therapy may need to increase their thyroid dose if estrogens or estrogen-containing oral contraceptives are given.

DRUG AND OR LABORATORY TEST INTERACTIONS

Drug/Laboratory Test Interactions —The following drugs or moieties are known to interfere with laboratory tests performed in patients on thyroid hormone therapy: androgens, corticosteroids, estrogens, oral contraceptives containing estrogens, iodine-containing preparations, and the numerous preparations containing salicylates.

1. Changes in TBg concentration should be taken into consideration in the interpretation of T4and T3values. In such cases, the unbound (free) hormone should be measured. Pregnancy, estrogens, and estrogen-containing oral contraceptives increase TBg concentrations. TBg may also be increased during infectious hepatitis. Decreases in TBg concentrations are observed in nephrosis, acromegaly, and after androgen or corticosteroid therapy. Familial hyper- or hypothyroxine-binding-globulinemias have been described. The incidence of TBg deficiency approximates 1 in 9,000. The binding of levothyroxine by TBPA is inhibited by salicylates.

2. Biotin supplementation is known to interfere with thyroid hormone immunoassays that are based on a biotin and streptavidin interaction, which may result in erroneous thyroid hormone test results. Stop biotin and biotin-containing supplements for at least 2 days prior to thyroid testing.

3. Medicinal or dietary iodine interferes with all in vivo tests of radio-iodine uptake, producing low uptakes which may not be relative of a true decrease in hormone synthesis.

4. The persistence of clinical and laboratory evidence of hypothyroidism in spite of adequate dosage replacement indicates either poor patient compliance, poor absorption, excessive fecal loss, or inactivity of the preparation. Intracellular resistance to thyroid hormone is quite rare.

CARCINOGENESIS AND MUTAGENESIS AND IMPAIRMENT OF FERTILITY

Carcinogenesis, Mutagenesis, and Impairment of Fertility— A reportedly apparent association between prolonged thyroid therapy and breast cancer has not been confirmed and patients on thyroid for established indications should not discontinue therapy. No confirmatory long-term studies in animals have been performed to evaluate carcinogenic potential, mutagenicity, or impairment of fertility in either males or females.

PREGNANCY

Pregnancy — Thyroid hormones do not readily cross the placental barrier. The clinical experience to date does not indicate any adverse effect on fetuses when thyroid hormones are administered to pregnant women. On the basis of current knowledge, thyroid replacement therapy to hypothyroid women should not be discontinued during pregnancy.

NURSING MOTHERS

Nursing Mothers— Minimal amounts of thyroid hormones are excreted in human milk. Thyroid is not associated with serious adverse reactions and does not have a known tumorigenic potential. However, caution should be exercised when thyroid is administered to a nursing woman.

PEDIATRIC USE

Pediatric Use — Pregnant mothers provide little or no thyroid hormone to the fetus. The incidence of congenital hypothyroidism is relatively high (1:4,000) and the hypothyroid fetus would not derive any benefit from the small amounts of hormone crossing the placental barrier. Routine determinations of serum T4and/or TSH is strongly advised in neonates in view of the deleterious effects of thyroid deficiency on growth and development.

Treatment should be initiated immediately upon diagnosis, and maintained for life, unless transient hypothyroidism is suspected; in which case, therapy may be interrupted for 2 to 8 weeks after the age of 3 years to reassess the condition. Cessation of therapy is justified in patients who have maintained a normal TSH during those 2 to 8 weeks.

ADVERSE REACTIONS

Adverse reactions other than those indicative of hyperthyroidism because of therapeutic overdosage, either initially or during the maintenance period, are rare (See OVERDOSAGE).

OVERDOSAGE

Signs and Symptoms- Excessive doses of thyroid result in a hypermetabolic state resembling in every respect the condition of endogenous origin. The condition may be self-induced.

Treatment of Overdosage- Dosage should be reduced or therapy temporarily discontinued if signs and symptoms of overdosage appear. Treatment may be reinstituted at a lower dosage. In normal individuals, normal hypothalamic-pituitary-thyroid axis function is restored in 6 to 8 weeks after thyroid suppression.

Treatment of acute massive thyroid hormone overdosage is aimed at reducing gastrointestinal absorption of the drugs and counteracting central and peripheral effects, mainly those of increased sympathetic activity. Vomiting may be induced initially if further gastrointestinal absorption can reasonably be prevented and barring contraindications such as coma, convulsions, or loss of the gagging reflex. Treatment is symptomatic and supportive. Oxygen may be administered and ventilation maintained. Cardiac glycosides may be indicated if congestive heart failure develops. Measures to control fever, hypoglycemia, or fluid loss should be instituted if needed. Antiadrenergic agents, particularly propranolol, have been used advantageously in the treatment of increased sympathetic activity. Propranolol may be administered intravenously at a dosage of 1 to 3 mg, over a 10-minute period or orally, 80 to 160 mg/day, initially, especially when no contraindications exist for its use.

Other adjunctive measures may include administration of cholestyramine to interfere with thyroxine absorption, and glucocorticoids to inhibit conversions of T4to T3.

DOSAGE AND ADMINISTRATION

The dosage of thyroid hormones is determined by the indication and must in every case be individualized according to patient response and laboratory findings.

Biotin supplementation may interfere with immunoassays for TSH, T4, and T3, resulting in erroneous thyroid hormone test results. Inquire whether patients are taking biotin or biotin-containing supplements. If so, advise them to stop biotin supplementation at least 2 days before assessing TSH and/or T4levels (see PRECAUTIONS).

Thyroid hormones are given orally. In acute, emergency conditions, injectable levothyroxine sodium may be given intravenously when oral administration is not feasible or desirable, as in the treatment of myxedema coma, or during total parenteral nutrition. Intramuscular administration is not advisable because of reported poor absorption.

Hypothyroidism- Therapy is usually instituted using low doses, with increments which depend on the cardiovascular status of the patient. The usual starting dose is 30 mg NP Thyroid®, with increments of 15 mg every 2 to 3 weeks. A lower starting dosage, 15 mg/day, is recommended in patients with long standing myxedema, particularly if cardiovascular impairment is suspected, in which case extreme caution is recommended. The appearance of angina is an indication for a reduction in dosage. Most patients require 60 to 120 mg/day. Failure to respond to doses of 180 mg suggests lack of compliance or malabsorption. Maintenance dosages 60 to 120 mg/day usually result in normal serum levothyroxine (T4) and triiodothyronine (T3) levels. Adequate therapy usually results in normal TSH and T4levels after 2 to 3 weeks of therapy.

Readjustment of thyroid hormone dosage should be made within the first four weeks of therapy, after proper clinical and laboratory evaluations, including serum levels of T4, bound and free, and TSH.

T3may be used in preference to levothyroxine (T4) during radio-isotope scanning procedures, since induction of hypothyroidism in those cases is more abrupt and can be of shorter duration. It may also be preferred when impairment of peripheral conversion of T4and T3is suspected.

Myxedema Coma- Myxedema coma is usually precipitated in the hypothyroid patient of long-standing by intercurrent illness or drugs such as sedatives and anesthetics and should be considered a medical emergency. Therapy should be directed at the correction of electrolyte disturbances and possible infection besides the administration of thyroid hormones. Corticosteroids should be administered routinely. T4and T3may be administered via a nasogastric tube but the preferred route of administration of both hormones is intravenous. Levothyroxine sodium (T4) is given at starting dose of 400 mcg (100 mcg/mL) given rapidly, and is usually well tolerated, even in the elderly. This initial dose is followed by daily supplements of 100 to 200 mcg given intravenously. Normal T4levels are achieved in 24 hours followed in 3 days by threefold elevation of T3. Oral therapy with thyroid hormone would be resumed as soon as the clinical situation has been stabilized and the patient is able to take oral medication.

Thyroid Cancer- Exogenous thyroid hormone may produce regression of metastases from follicular and papillary carcinoma of the thyroid and is used as ancillary therapy of these conditions with radioactive iodine. TSH should be suppressed to low or undetectable levels. Therefore, larger amounts of thyroid hormone than those used for replacement therapy are required. Medullary carcinoma of the thyroid is usually unresponsive to this therapy.

Thyroid Suppression Therapy- Administration of thyroid hormone in doses higher than those produced physiologically by the gland results in suppression of the production of endogenous hormone. This is the basis for the thyroid suppression test and is used as an aid in the diagnosis of patients with signs of mild hyperthyroidism in whom base line laboratory tests appear normal, or to demonstrate thyroid gland autonomy in patients with Graves ophthalmopathy. 131I uptake is determined before and after the administration of the exogenous hormone. A 50% or greater suppression of uptake indicates a normal thyroid-pituitary axis and thus rules out thyroid gland autonomy.

For adults, the usual suppressive dose of levothyroxine (T4) is 1.56 mcg/kg of body weight per day given for 7 to 10 days. These doses usually yield normal serum T4and T3levels and lack of response to TSH.

Thyroid hormones should be administered cautiously to patients in whom there is strong suspicion of thyroid gland autonomy, in view of the fact that the exogenous hormone effects will be additive to the endogenous source.

Pediatric Dosage- Pediatric dosage should follow the recommendations summarized in Table 1. In infants with congenital hypothyroidism, therapy with full doses should be instituted as soon as the diagnosis has been made.

Recommended Pediatric Dosage for Congenital Hypothyroidism
 | NP Thyroid® Tablets
Age | Dose per day | Daily dose per kg of body weight
0 - 6 mos. | 15 - 30 mg | 4.8 - 6 mg
6 - 12 mos. | 30 - 45 mg | 3.6 - 4.8 mg
1 - 5 yrs. | 45 - 60 mg | 3 - 3.6 mg
6 - 12 yrs. | 60 - 90 mg | 2.4 - 3 mg
Over 12 yrs. | Over 90 mg | 1.2 - 1.8 mg

HOW SUPPLIED

NP Thyroid®tablets (thyroid tablets, USP) are available as:

- 15 mg (1/4 gr)
  - NDC 42192-327-30 in 30-count bottle
  - NDC 42192-327-90 in 90-count bottle
  - NDC 42192-327-01 in 100-count bottle

- 30 mg (1/2 gr)
  - NDC 42192-329-30 in 30-count bottle
  - NDC 42192-329-90 in 90-count bottle
  - NDC 42192-329-01 in 100-count bottle
  - NDC 42192-329-10 in 1000-count bottle

- 60 mg (1 gr)
  - NDC 42192-330-30 in 30-count bottle
  - NDC 42192-330-90 in 90-count bottle
  - NDC 42192-330-01 in 100-count bottle
  - NDC 42192-330-10 in 1000-count bottle

- 90 mg (1 1/2 gr)
  - NDC 42192-331-30 in 30-count bottle
  - NDC 42192-331-90 in 90-count bottle
  - NDC 42192-331-01 in 100-count bottle
  - NDC 42192-331-10 in 1000-count bottle

- 120 mg (2 gr)
  - NDC 42192-328-30 in 30-count bottle
  - NDC 42192-328-90 in 90-count bottle
  - NDC 42192-328-01 in 100-count bottle

NP Thyroid®tablets are available in the following strengths:

- 15 mg (1/4 grain) - tan, oval-shaped tablet, debossed on one side with “AP” and “327” on the other side.
- 30 mg (1/2 grain) – tan, round tablet, debossed on one side with “AP” and “329” on the other side.
- 60 mg (1 grain) – tan, round tablet, debossed on one side with “AP” and “330” on the other side.
- 90 mg (1 1/2 grain) – tan, round tablet, debossed on one side with “AP” and “331” on the other side.
- 120 mg (2 grain) – tan, round tablet, debossed on one side with “AP” and “328” on the other side.

STORAGE AND HANDLING

Store in a tight container protected from light and moisture. Store between 15° - 30°C (59° - 86°F).

All prescription substitutions and/or recommendations using this product shall be made subject to state and federal statutes as applicable.

Please note: This is not an Orange Book product and has not been subjected to FDA therapeutic equivalency or other equivalency testing. No representation is made as to generic status or bioequivalency.Each person recommending a prescription substitution using this product shall make such recommendations based on each such person’s professional opinion and knowledge, upon evaluating the active ingredients, excipients, inactive ingredients and chemical information provided herein.

MANUFACTURED FOR:
Acella Pharmaceuticals, LLC
Alpharetta, GA 30005
1-800-541-4802
L-0440 Rev 0924-01

PACKAGE LABEL

NDC 42192-327-01

NP Thyroid®
(Thyroid Tablets, USP)

1/4 grain (15 mg)

Rx Only 100 Tablets

EACH TABLET CONTAINS:
levothyroxine (T4)...........................9.5 mcgliothyronine (T3)............................2.25 mcg

DIRECTIONS FOR USE: See Insert.
USUAL DOSE: 15 mg - 180 mg once a day.NP Thyroid is a natural product with a strong, characteristic odor.Store in a tight container protected from light and moisture.
Store between 15° - 30°C (59° - 86°F).

MANUFACTURED FOR:
Acella Pharmaceuticals, LLC
Alpharetta, GA 30009
1-800-541-4802

Lot #/Exp. Date:

PACKAGE LABEL

NDC 42192-329-01

NP Thyroid®
(Thyroid Tablets, USP)

1/2 grain (30 mg)

Rx Only 100 Tablets

EACH TABLET CONTAINS:

levothyroxine (T4)...........................19 mcg
liothyronine (T3)............................4.5 mcg

DIRECTIONS FOR USE: See Insert.

USUAL DOSE: 15 mg - 180 mg once a day.

NP Thyroid is a natural product with a strong, characteristic odor.

Store in a tight container protected from light and moisture. Store between 15° - 30°C (59° - 86°F).

MANUFACTURED FOR:
Acella Pharmaceuticals, LLC
Alpharetta, GA 30009
1-800-541-4802

Lot #/Exp. Date:

PACKAGE LABEL

NDC 42192-330-01

NP Thyroid®
(Thyroid Tablets, USP)

1 grain (60 mg)

Rx Only 100 Tablets

EACH TABLET CONTAINS:

levothyroxine (T4)...........................38 mcg
liothyronine (T3)............................9 mcg

DIRECTIONS FOR USE: See Insert.

USUAL DOSE: 15 mg - 180 mg once a day.

NP Thyroid is a natural product with a strong, characteristic odor.

Store in a tight container protected from light and moisture. Store between 15° - 30°C (59° - 86°F).

MANUFACTURED FOR:
Acella Pharmaceuticals, LLC
Alpharetta, GA 30009
1-800-541-4802

Lot #/Exp. Date:

PACKAGE LABEL

NDC 42192-331-01

NP Thyroid®
(Thyroid Tablets, USP)

1 and 1/2 grain (90 mg)

Rx Only 100 Tablets

EACH TABLET CONTAINS:

levothyroxine (T4)...........................57 mcg
liothyronine (T3)............................13.5 mcg

DIRECTIONS FOR USE: See Insert.

USUAL DOSE: 15 mg - 180 mg once a day.

NP Thyroid is a natural product with a strong, characteristic odor.

Store in a tight container protected from light and moisture. Store between 15° - 30°C (59° - 86°F).

MANUFACTURED FOR:
Acella Pharmaceuticals, LLC
Alpharetta, GA 30009
1-800-541-4802

Lot #/Exp. Date:

PACKAGE LABEL

NDC 42192-328-01

NP Thyroid®
(Thyroid Tablets, USP)

2 grain (120 mg)

Rx Only 100 Tablets

EACH TABLET CONTAINS:

levothyroxine (T4)...........................76 mcg
liothyronine (T3)............................18 mcg

DIRECTIONS FOR USE: See Insert.

USUAL DOSE: 15 mg - 180 mg once a day.

NP Thyroid is a natural product with a strong, characteristic odor.

Store in a tight container protected from light and moisture.

Store between 15° - 30°C (59° - 86°F).

MANUFACTURED FOR:
Acella Pharmaceuticals, LLC
Alpharetta, GA 30009
1-800-541-4802

Lot #/Exp. Date: